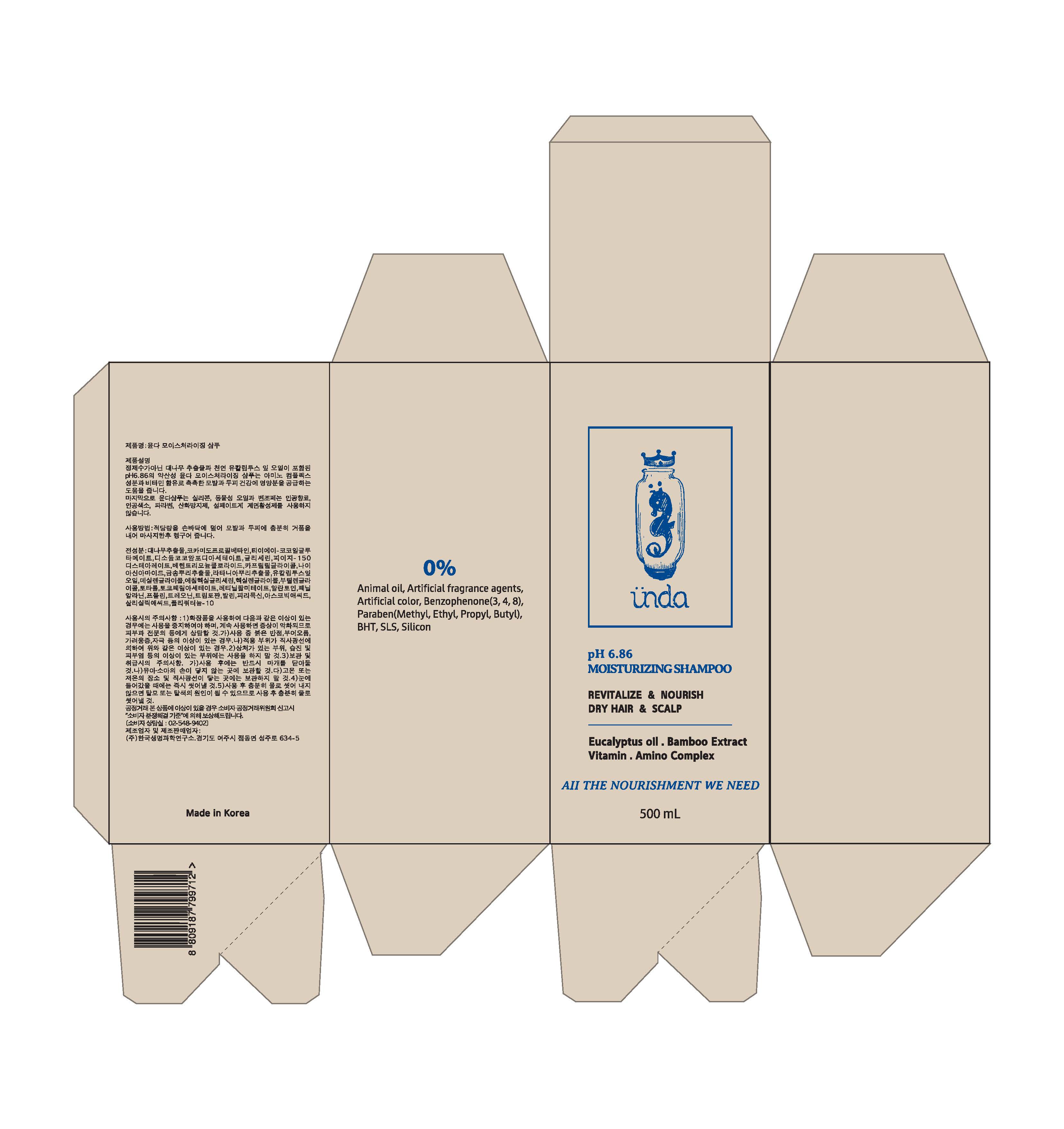 DRUG LABEL: UNDA MOSITURIZING
NDC: 70845-0011 | Form: SHAMPOO
Manufacturer: UNDA
Category: otc | Type: HUMAN OTC DRUG LABEL
Date: 20160725

ACTIVE INGREDIENTS: SALICYLIC ACID 0.001 g/100 mL; EUCALYPTUS GLOBULUS LEAF 0.1 g/100 mL; BAMBUSA VULGARIS TOP 53.13 g/100 mL
INACTIVE INGREDIENTS: DIPROPYLENE GLYCOL; ALLANTOIN

Drug Facts

ACTIVE INGREDIENT

Salicylic Acid, Bambusa Vulgaris Extract, Eucalyptus Globulus Leaf Oil

INACTIVE INGREDIENT

Cocamidopropyl Betaine, TEA-Cocoyl Glutamate, Disodium Cocoamphodiacetate, Glycerin, PEG-150 Distearate, Behentrimonium Chloride, Caprylyl Glycol, Niacinamide, Sciadopitys Verticillata Root Extract, Krameria Triandra Root Extract, Decylene Glycol, Ethylhexylglycerin, Hexylene Glycol, Butylene Glycol, Totarol, Tocopheryl Acetate, Retinyl Palmitate, Allantoin, Phenylalanine, Proline, Threonine, Tryptophan, Valine, Pyridoxine, Ascorbic Acid, Polyquaternium-10

PURPOSE

Helps alleviate the concerns such as hair loss, dandruff, and dryness.

keep out of reach of the children

INDICATIONS AND USAGE

1. Wet your hair with plenty of lukewarm water.
2. Use one pump of Ünda moisturizing shampoo.
3. Using the tip of your fingertips, rub the shampoo into your hair and make plenty of bubbles.
4. Enjoy its natural scent and massage your scalp for 2~3 minutes
5. Wash off with lukewarm water
6. Dry your hair with a dry towel
7. Hair Dry

WARNINGS

1. Do not use in the following cases(Eczema and scalp wounds)
2.Side Effects
1)Due to the use of this product if rash, irritation, itching and symptopms of hypersnesitivity occur, dicontinue use and consult your phamacisr or doctor
3.General Precautions
1)If in contact with the eyes, wash out thoroughty with water If the symptoms are servere, seek medical advice immediately
2)This product is for exeternal use only. Do not use for internal use
4.Storage and handling precautions
1)If possible, avoid direct sunlight and store in cool and area of low humidity
2)In order to maintain the quality of the product and avoid misuse
3)Avoid placing the product near fire and store out in reach of children

DOSAGE AND ADMINISTRATION

for external use only